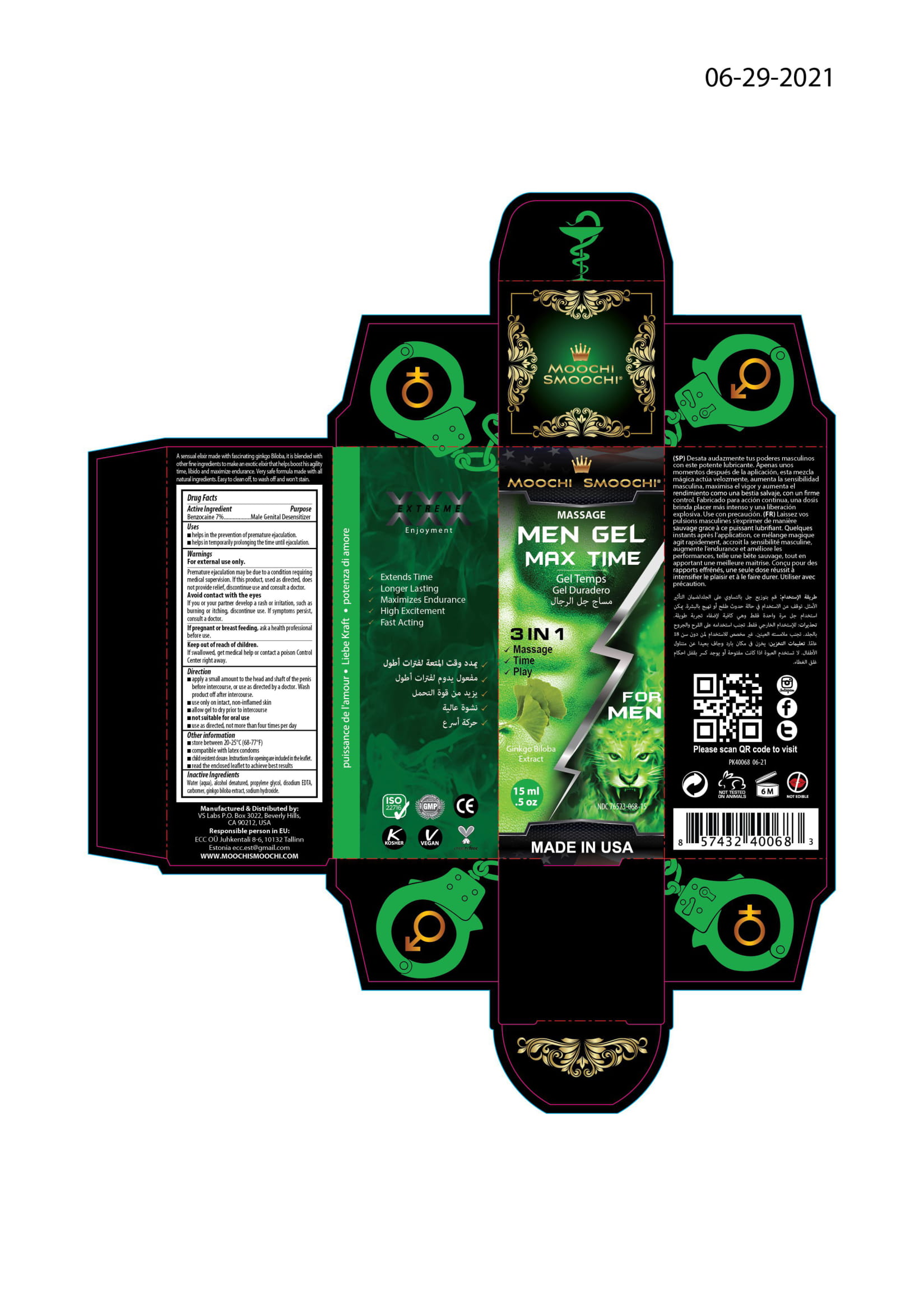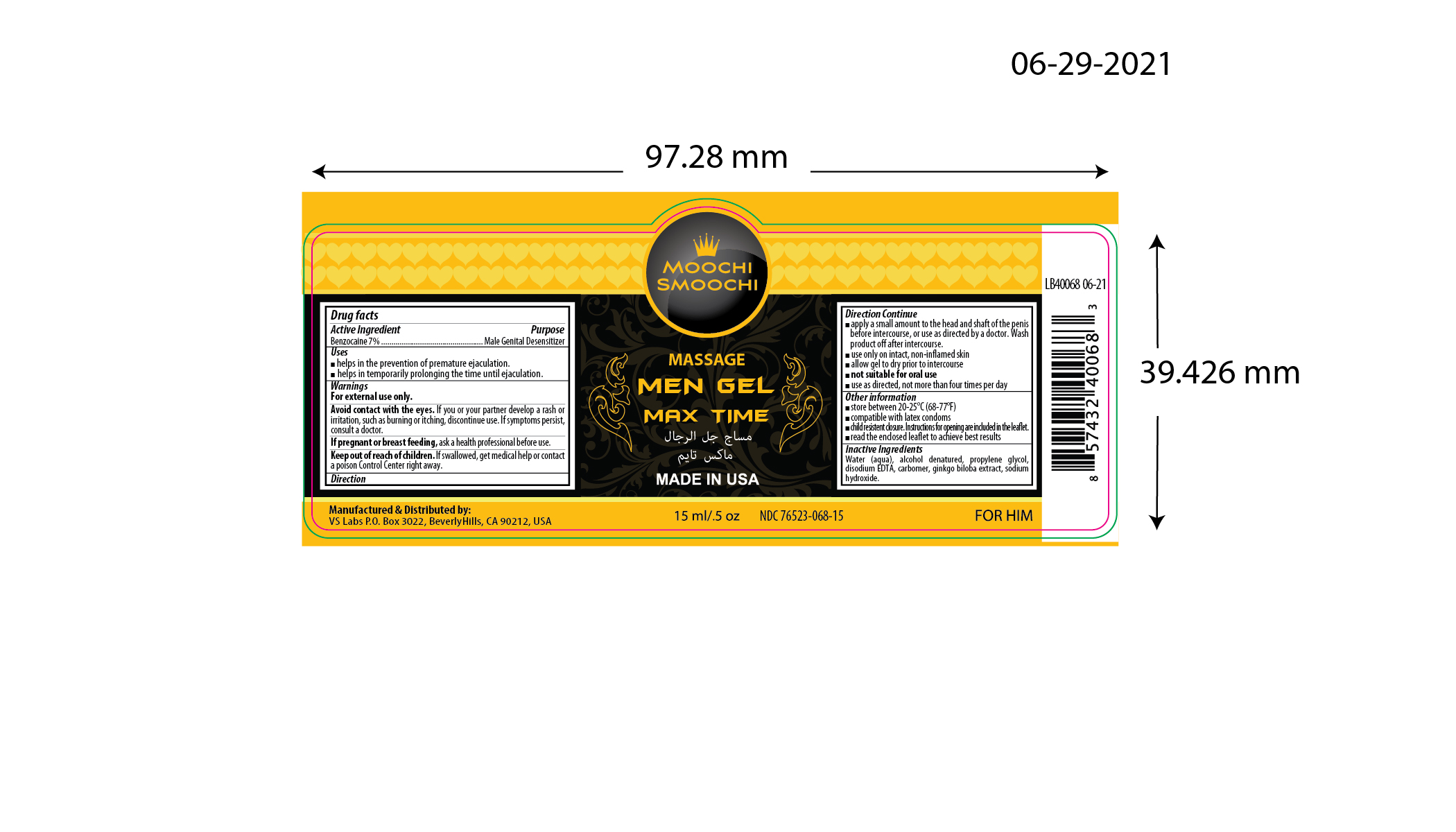 DRUG LABEL: Massage Men Gel Max Time
NDC: 76523-068 | Form: GEL
Manufacturer: Valley of the Sun Cosmetics LLC
Category: otc | Type: HUMAN OTC DRUG LABEL
Date: 20210702

ACTIVE INGREDIENTS: BENZOCAINE 7 g/100 g
INACTIVE INGREDIENTS: SODIUM HYDROXIDE; WATER; PROPANEDIOL; CARBOMER 940; GINKGO; EDETATE DISODIUM; ALCOHOL

Massage Men Gel Max Time

Active Ingredient

Benzocaine 7%

Purpose

Male Genital Desensitizer

Uses

- helps in the prevention of premature ejaculation
- helps in temporarily prolonging the time until ejaculation

Warning

For external use only

When using this product

Avoid contact with eyes

Stop use and ask doctor

- Premature ejaculation may be due to a condition requiring medical supervision. If this product, used as directed, does not provide relief, discontinue use and consult a doctor.
- If you or your partner develop rash or irritation, such as burning or itching, discontinue use. If symptoms persist, consult a doctor.

If pregnant or breast feeding, ask a health professional before use.

Keep out of reach of children

If swallowed, get medical help, or contact a poison control center right away.

Directions

- apply a small amount to the head and shaft of the penis before intercourse or use as directed by a doctor. Wash product off after intercourse.
- use only on intact, non-inflamed skin
- allow gel to dry prior to intercourse
- not suitable for oral use
- use as directed, not more than four times per day

Other information

- Store between 20-25°C (68-77°F)
- Compatible with latex condoms
- Children resistant closure. Instructions for opening are included in the leaflet
- Read the enclosed leaflet to achieve best results

Inactive Ingredients

Water (aqua), alcohol denatured, propylene glycol, disodium EDTA, carbomer, ginkgo biloba (ginkgo) extract, sodium hydroxide